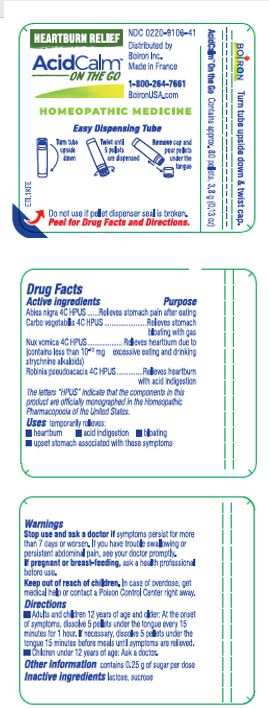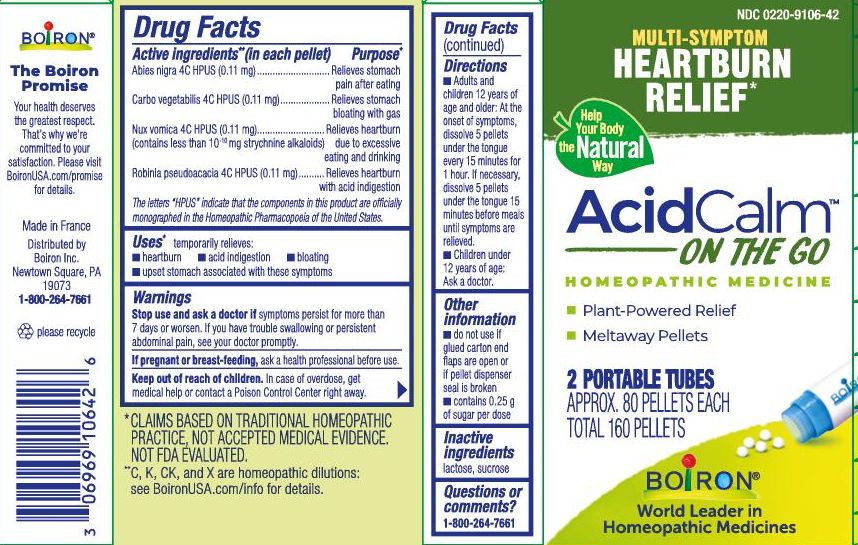 DRUG LABEL: AcidCalm
NDC: 0220-9106 | Form: PELLET
Manufacturer: Boiron
Category: homeopathic | Type: HUMAN OTC DRUG LABEL
Date: 20250215

ACTIVE INGREDIENTS: ROBINIA PSEUDOACACIA BARK 4 [hp_C]/1 1; ACTIVATED CHARCOAL 4 [hp_C]/1 1; STRYCHNOS NUX-VOMICA SEED 4 [hp_C]/1 1; PICEA MARIANA RESIN 4 [hp_C]/1 1
INACTIVE INGREDIENTS: LACTOSE, UNSPECIFIED FORM; SUCROSE

AcidCalm pellets

Active ingredients** (in each pellet)

Abies nigra 4C HPUS (0.11 mg)

Carbo vegetabilis 4C HPUS (0.11 mg)

Nux vomica 4C HPUS (0.11 mg) (contains less than 10^-10 mg strychnine alkaloids)

Robinia pseudoacacia 4C HPUS (0.11 mg)

The letters "HPUS" indicate that the components in this product are officially monographed in the Homeopathic Pharmacopoeia of the United States.

Purpose*

Abies nigra 4C HPUS (0.11 mg) ... Relieves stomach pain after eating

Carbo vegetabilis 4C HPUS (0.11 mg) ... Relieves stomach bloating with gas

Nux vomica 4C HPUS (0.11 mg) ... Relieves heartburn due to excessive eating and drinking

Robinia pseudoacacia 4C HPUS (0.11 mg) ... Relieves heartburn with acid indigestion

Uses*

temporarily relieves:

heartburn
acid indigestion
bloating
upset stomach associated with these symptoms

Stop use and ask a doctor if symptoms persist for more than 7 days or worsen. If you have trouble swallowing or persistent abdominal pain, see your doctor promptly.

PREGNANCY OR BREAST FEEDING

If pregnant or breast-feeding, ask a health professional before use.

Keep out of reach of children. In case of overdose, get medical help or contact a Poison Control Center right away.

Directions

- Adults and children 12 years of age and older: At the onset of symptoms, dissolve 5 pellets under the tongue every 15 minutes for 1 hour. If necessary, dissolve 5 pellets under the tongue 15 minutes before meals until meals until symptoms are relieved.
- Children under 12 years of age: Ask a doctor.

INACTIVE INGREDIENT

lactose, sucrose

QUESTIONS

1-800-264-7661

Made in France

Distributed by

Boiron, Inc.

Newtown Square, PA 19073

- do not use if glued carton end flaps are open or if pellet dispenser seal is broken
- contains 0.25 g of sugar per dose

MULTI-SYMPTOM

HEARTBURN RELIEF*

2 PORTABLE TUBES

APPROX. 80 PELLETS EACH

TOTAL 160 PELLETS

Plant-Powered Relief

Meltaway Pellets

Contains approx. 80 pellets, 3.8 g (0.13 oz)

Turn tube upside down

Twist until 5 pellets are dispensed

Remov cap and pour pellets under the tongue

*CLAIMS BASED ON TRADITIONAL HOMEOPATHIC PRACTICE NOT ACCEPTED MEDICAL EVIDENCE. NOT FDA EVALUATED.
**C,K,CK, and X are homeopathic dilutions: see BoironUSA.com/info for details.